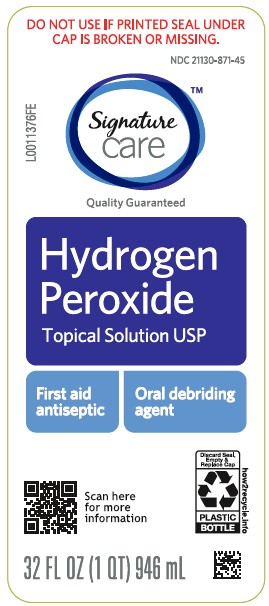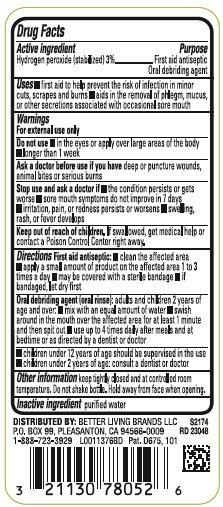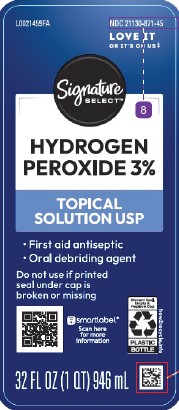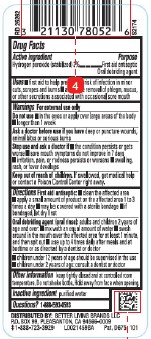 DRUG LABEL: Hydrogen Peroxide
NDC: 21130-871 | Form: SOLUTION
Manufacturer: Better Living Brands, LLC
Category: otc | Type: HUMAN OTC DRUG LABEL
Date: 20260224

ACTIVE INGREDIENTS: HYDROGEN PEROXIDE 30 mg/1 mL
INACTIVE INGREDIENTS: WATER

Signature Care_Signature Select 871.001/871AA
3% Hydrogen Peroxide

Active ingredient

Hydrogen peroxide (stabilized) 3%

purpose

First Aid Antiseptic

Oral debriding agent

Uses

- first aid to help prevent the risk of infection in minor cuts, scrapes and burns
- aids in the removal of phlegm, mucus, or other secretions associated with occasional sore mouth

Warnings

For external use only

Do Not Use

- in the eyes or apply over large areas of the body
- longer than 1 week

Ask a doctor before use if you have

deep or puncture wounds, animal bites or serious burns

Stop use and ask a doctor if

- the condition persists or gets worse
- sore mouth symptoms do not improve in 7 days
- irritation, pain, or redness persists or worsens
- swelling, rash, or fever develops

Keep out of reach of children.

If swallowed, get medical help or contact a Poison Control Center right away.

Directions

First Aid Antiseptic:

- clean the affected area
- apply a small amount of the product on the affected area 1 to 3 times a day
- may be covered with a sterile bandage
- if bandaged, let dry first

Oral Debriding Agent (oral rinse): adults and children over 2 years of age

- mix with equal amount of water
- swish around in the mouth over the affected area for at least 1 minute, then spit out
- use up to 4 times daily after meals and at bedtime or as directed by a dentist or doctor

- children under 12 years of age should be supervised in the use
- children under 2 years of age: consult a dentist or doctor

Other information

Keep tightly closed and at controlled room temperature. Do not shake bottle. Hold away from face when opening.

Inactive ingredient

purified water

Questions?

1-888-593-0593

ADVERSE REACTION

DISTRIBUTED BY: BETTER LIVING BRANDS LLC

P.O. BOX 99 PLEASANTON, CA 94566-0009

1-888-723-3929

Pat. D675, 101

Principal Display Panel

NDC 21130-871-45

LOVE IT OR IT'S ON US‡

Signature Select™

HYDROGEN PEROXIDE 3%

TOPICAL SOLUTION USP

- First aid antiseptic
- Oral debriding agent

Do not use is printed seal under cap is broken or missing

smartlabel Scan here for more information

Discard Seal, Empty & Replace cap

PLASTIC BOTTLE

how2recycle.info

32 FL OZ (1 QT) 946 mL

Principal display panel

DO NOT USE IF PRINTED SEAL UNDER CAP IS BROKEN OR MISSING

NDC 21130-871-45

Signature Care™

Quality Guaranteed

Hydrogen Peroxide

Topical Solution USP

First Aid Antiseptic

Oral debriding agent

Scan here for more information

how2recycle.info

Discard Seal, Empty & Replace Cap

PLASTIC BOTTLE

32 FL OZ (1 QT) 946 mL